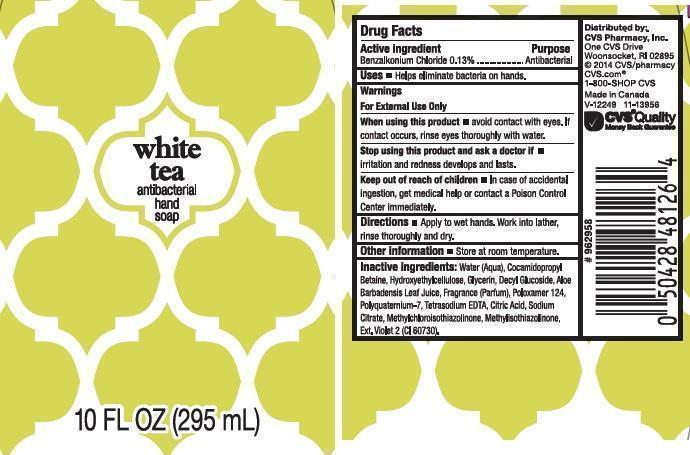 DRUG LABEL: CVS
NDC: 59779-272 | Form: LIQUID
Manufacturer: CVS PHARMACY
Category: otc | Type: HUMAN OTC DRUG LABEL
Date: 20140423

ACTIVE INGREDIENTS: BENZALKONIUM CHLORIDE 1.3 mg/1 mL
INACTIVE INGREDIENTS: WATER; COCAMIDOPROPYL BETAINE; HYPROMELLOSES; GLYCERIN; DECYL GLUCOSIDE; ALOE VERA LEAF; POLOXAMER 124; POLYQUATERNIUM-7 (70/30 ACRYLAMIDE/DADMAC; 1600000 MW); EDETATE SODIUM; CITRIC ACID MONOHYDRATE; SODIUM CITRATE; METHYLCHLOROISOTHIAZOLINONE; METHYLISOTHIAZOLINONE; EXT. D&C VIOLET NO. 2

DRUG FACTS

ACTIVE INGREDIENT

BENZALKONIUM CHLORIDE 0.13%

PURPOSE

ANTIBACTERIAL

USES

HELPS ELIMINATE BACTERIA ON HANDS

WARNINGS

FOR EXTERNAL USE ONLY

WHEN USING THIS PRODUCT

AVOID CONTACT WITH EYES. IF CONTACT OCCURS, RINSE EYES THOROUGHLY WITH WATER

STOP USING THIS PRODUCT AND ASK A DOCTOR IF

IRRITATION AND REDNESS DEVELOPS AND LASTS

KEEP OUT OF REACH OF CHILDREN

IN CASE OF ACCIDENTAL INGESTION, GET MEDICAL HELP OR CONTACT A POISON CONTROL CENTER IMMEDIATELY

DIRECTIONS

APPLY TO WET HANDS. WORK INTO LATHER, RINSE THOROUGHLY AND DRY

OTHER INFORMATION

STORE AT ROOM TEMPERATURE

INACTIVE INGREDIENTS

WATER (AQUA), COCAMIDOPROPYL BETAINE, HYDROXYETHYLCELLULOSE, GLYCERIN, DECYL GLUCOSIDE, ALOE BARBADENSIS LEAF JUICE, FRAGRANCE (PARFUM), POLOXAMER 124, POLYQUATERNIUM-7, TETRASODIUM EDTA, CITRIC ACID, SODIUM CITRATE, METHYLCHLOROISOTHIAZOLINONE, METHYLISOTHIAZOLINONE, EXT. VIOLET 2 (CI 60730)